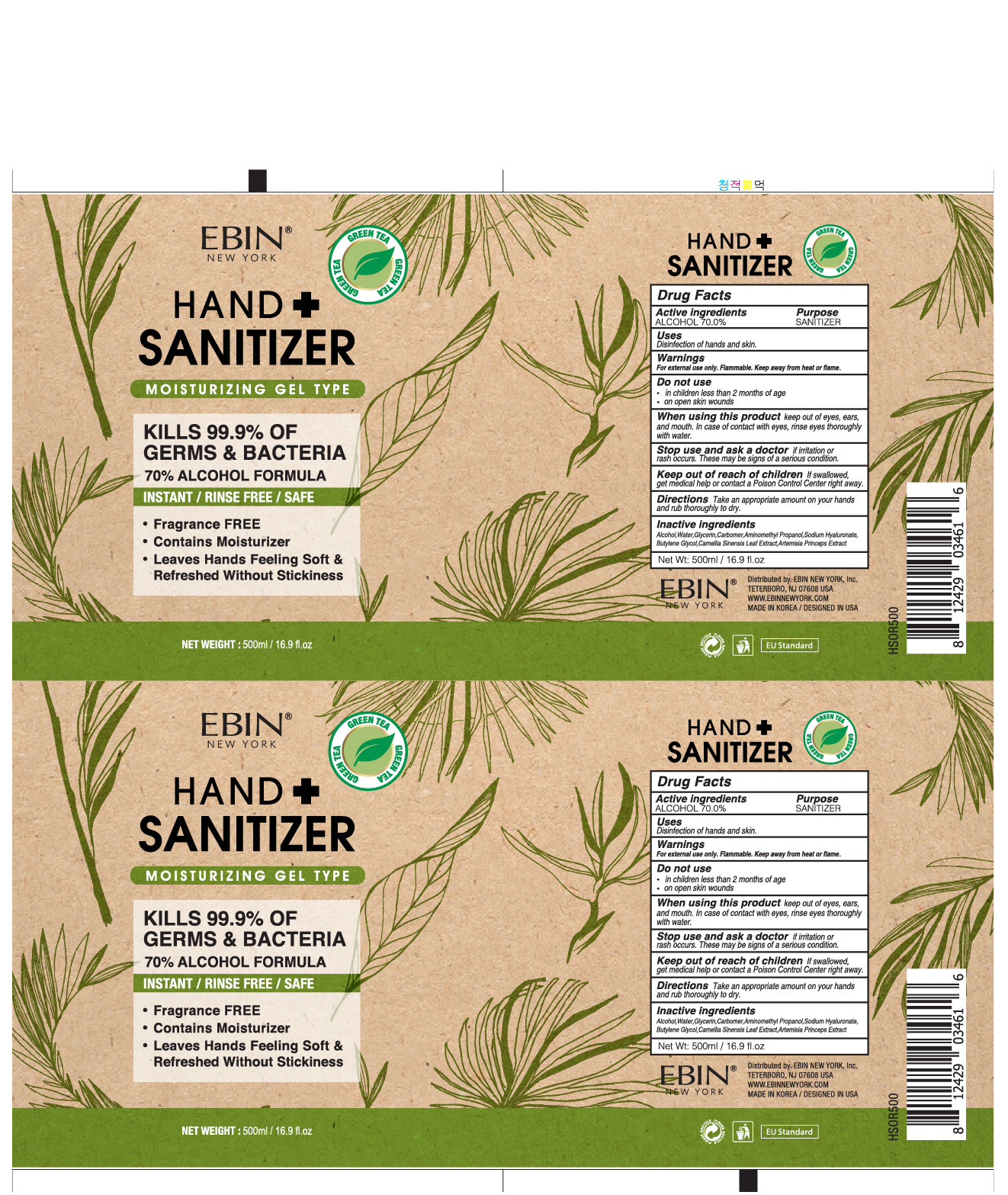 DRUG LABEL: EBIN NEW YORK HAND PLUS SANITIZER
NDC: 73823-716 | Form: GEL
Manufacturer: WHAIN COSMETIC
Category: otc | Type: HUMAN OTC DRUG LABEL
Date: 20200512

ACTIVE INGREDIENTS: ALCOHOL 350 mL/500 mL
INACTIVE INGREDIENTS: AMINOMETHYL PROPANEDIOL; GLYCERIN; HYALURONATE SODIUM; BUTYLENE GLYCOL; CARBOMER HOMOPOLYMER, UNSPECIFIED TYPE; WATER; ARTEMISIA PRINCEPS LEAF; GREEN TEA LEAF

EBIN NEW YORK HAND PLUS SANITIZER 500 ml : 73823-716